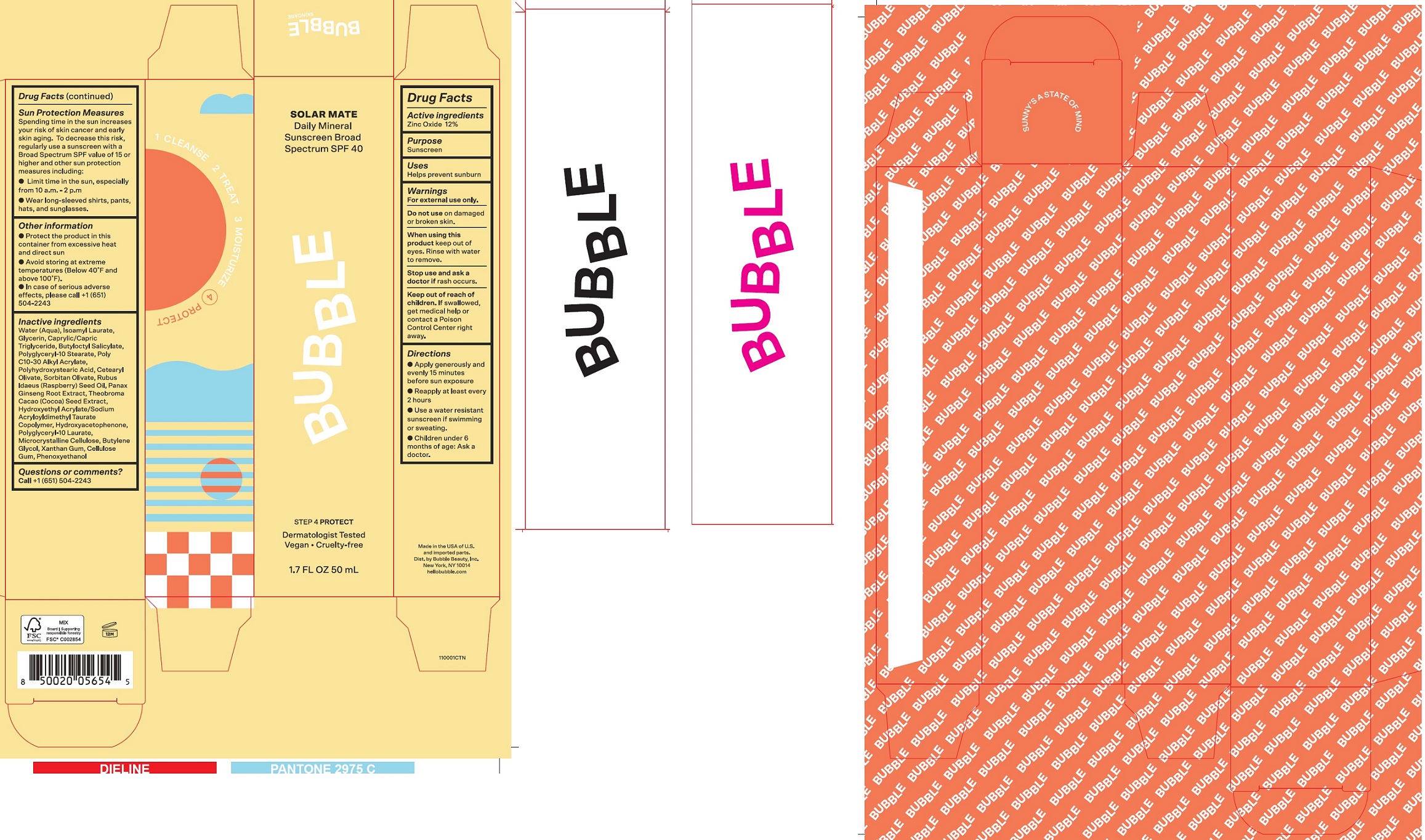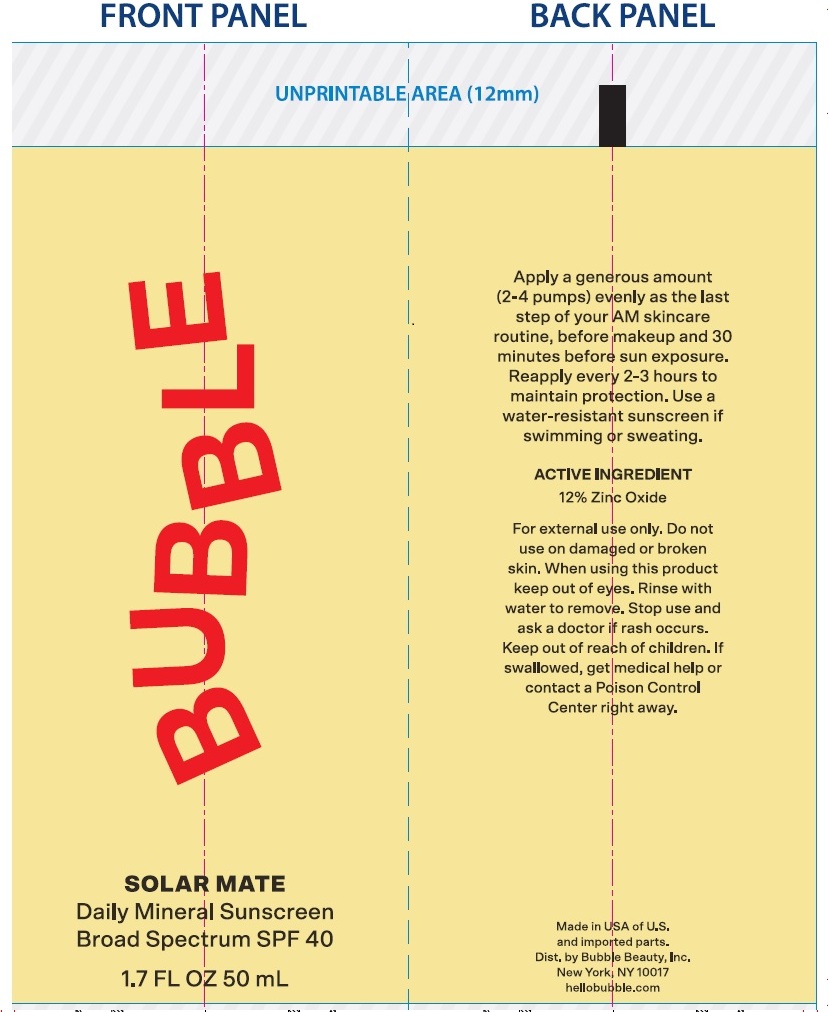 DRUG LABEL: Bubble Solar Mate Daily Mineral Sunscreen SPF 40
NDC: 83509-156 | Form: CREAM
Manufacturer: Bubble Beauty, Inc.
Category: otc | Type: HUMAN OTC DRUG LABEL
Date: 20250916

ACTIVE INGREDIENTS: ZINC OXIDE 120 mg/1 mL
INACTIVE INGREDIENTS: WATER; ISOAMYL LAURATE; GLYCERIN; MEDIUM-CHAIN TRIGLYCERIDES; BUTYLOCTYL SALICYLATE; POLYGLYCERYL-10 STEARATE; CETEARYL OLIVATE; SORBITAN OLIVATE; RASPBERRY SEED OIL; ASIAN GINSENG; COCOA; HYDROXYACETOPHENONE; POLYGLYCERYL-10 LAURATE; MICROCRYSTALLINE CELLULOSE; BUTYLENE GLYCOL; XANTHAN GUM; CELLULOSE GUM; PHENOXYETHANOL

Bubble Solar Mate Daily Mineral Sunscreen SPF 40

Active ingredients

Zinc Oxide 12%

Purpose

Sunscreen

Uses:

Helps prevent sunburn

Warnings

For external use only.

Do not use

on damaged or broken skin.

When using this product

keep out of eyes. Rinse with water to remove.

Stop use and ask a doctor if

rash occurs.

Keep out of reach of children

If swallowed, get medical help or contact a Poison Control Center right away.

Directions:

- Apply generously and evenly 15 minutes before sun exposure
- Reapply at least every 2 hours
- Use a water resistant sunscreen if swimming or sweating.
- Children under 6 months of age: Ask a doctor.
- Sun Protection Measures Spending time in the sun increases your risk of skin cancer and early skin aging. To decrease this risk, regularly use a sunscreen with a Broad Spectrum SPF value of 15 or higher and other sun protection measures including:
- Limit time in the sun, especially from 10 a.m. - 2 p.m.
- Wear long-sleeved shirts, pants, hats, and sunglasses.

Other information

- Protect the product in this container from excessive heat and direct sun
- Avoid storing at extreme temperatures (Below 40°F and above 100°F).
- In case of serious adverse effects, please call +1 (651) 504-2243

Inactive ingredients

Water (Aqua), Isoamyl Laurate, Glycerin, Caprylic/Capric Triglyceride, Butyloctyl Salicylate, Polyglyceryl-10 Stearate, Poly C10-30 Alkyl Acrylate, Polyhydroxystearic Acid, Cetearyl Olivate, Sorbitan Olivate, Rubus Idaeus (Raspberry) Seed Oil, Panax Ginseng Root Extract, Theobroma Cacao (Cocoa) Seed Extract, Hydroxyethyl Acrylate/Sodium Acryloyldimethyl Taurate Copolymer, Hydroxyacetophenone, Polyglyceryl-10 Laurate, Microcrystalline Cellulose, Butylene Glycol, Xanthan Gum, Cellulose Gum, Phenoxyethanol

Questions or comments?

Call+1(651) 504-2243